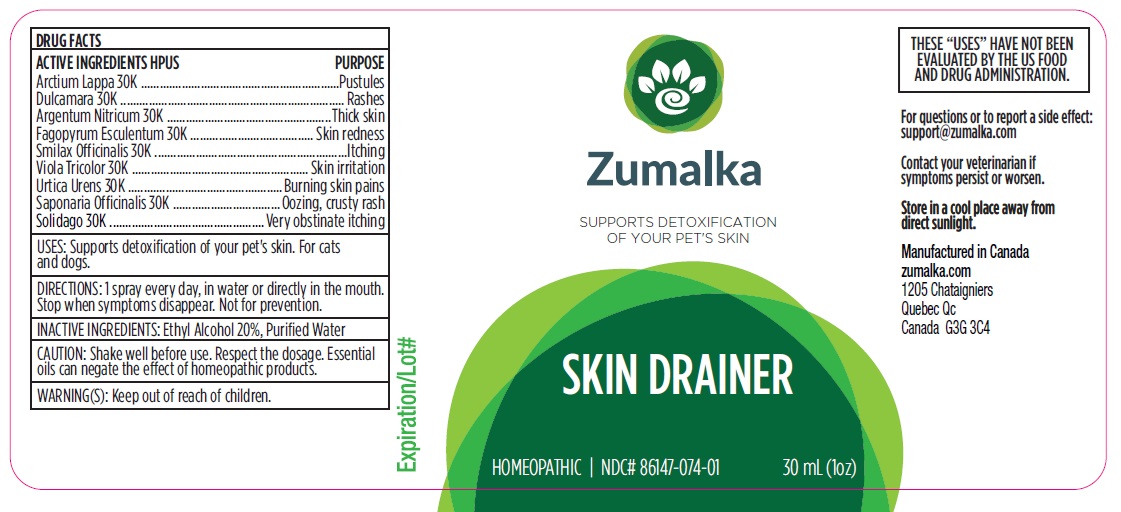 DRUG LABEL: SKIN DRAINER
NDC: 86147-074 | Form: LIQUID
Manufacturer: Groupe Cyrenne Inc.
Category: homeopathic | Type: OTC ANIMAL DRUG LABEL
Date: 20251120

ACTIVE INGREDIENTS: ARCTIUM LAPPA FRUIT 30 [kp_C]/30 mL; SOLANUM DULCAMARA WHOLE 30 [kp_C]/30 mL; SILVER NITRATE 30 [kp_C]/30 mL; FAGOPYRUM ESCULENTUM WHOLE 30 [kp_C]/30 mL; SMILAX OFFICINALIS WHOLE 30 [kp_C]/30 mL; VIOLA TRICOLOR WHOLE 30 [kp_C]/30 mL; URTICA URENS WHOLE 30 [kp_C]/30 mL; SAPONARIA OFFICINALIS ROOT 30 [kp_C]/30 mL; SOLIDAGO VIRGAUREA FLOWERING TOP 30 [kp_C]/30 mL
INACTIVE INGREDIENTS: ALCOHOL; WATER

Active ingredients

Arctium Lappa 30k, Dulcamara 30k, Argentum Nit 30k, Fagopyrum Esculentum 30k, Smilax Officinalis 30k, Viola Tricolor 30k, Urtica Urens 30k, Saponaria 30k, solidago virgaurea flowering top

Uses

Supports detoxification of your pet's skin. For cats and dogs.

Warnings

Shake well before use. Respect the dosage. Not for pets with cancer or young pets under the age of 2 years old. Keep out of reach of children.

Direction

1 spray every day, in water or directly in the mouth.

Inactive ingredients

Ethyl alcohol 20%, purified water

Other information

The letters "HPUS" indicate that the active ingredients are in the official Homeopathic Pharmacopoeia of the United States. Homeopathic remedy. Store at room temperature.